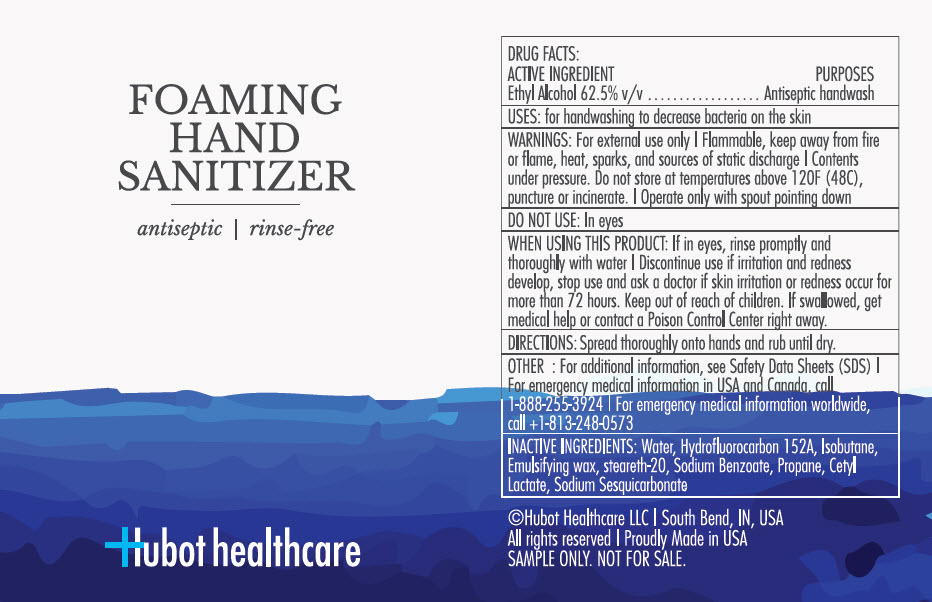 DRUG LABEL: HUBOT HEALTHCARE HAND SANITIZER
NDC: 72138-490 | Form: AEROSOL, FOAM
Manufacturer: HUBOT HEALTHCARE LLC.
Category: otc | Type: HUMAN OTC DRUG LABEL
Date: 20200311

ACTIVE INGREDIENTS: ALCOHOL 54.7 g/100 g
INACTIVE INGREDIENTS: WATER; 1,1-DIFLUOROETHANE; ISOBUTANE; STEARETH-20; SODIUM BENZOATE; PROPANE; CETYL LACTATE; SODIUM SESQUICARBONATE

AEROSOL FOAM HAND SANITIZER

Drug Facts

Active ingredient

Ethyl Alcohol 62.5% v/v

Purposes

Antiseptic handwash

Uses

for handwashing to decrease bacteria on the skin

Warnings

- For external use only
- Flammable, keep away from fire or flame, heat, sparks, and sources of static discharge
- Contents under pressure. Do not store at temperatures above 120F (48C), puncture or incinerate.
- Operate only with spout pointing down

Do not use

- In eyes

When using this product

- If in eyes, rinse promptly and thoroughly with water
- Discontinue use if irritation and redness develop

Stop use and ask a doctor if skin irritation or redness occur for more than 72 hours.

Keep out of reach of children. If swallowed, get medical help or contact a Poison Control Center right away.

Directions

- Spread thoroughly onto hands and rub until dry.

Other Information

- For additional information, see Safety Data Sheets (SDS)
- For emergency medical information in USA and Canada, call 1-888-255-3924
- For emergency medical information worldwide, call +1-813-248-0573

Inactive Ingredients

Water. Hydrofluorocarbon 152A, Isobutane, Emulsifying wax, steareth-20, Sodium Benzoate, Propane, Cetyl Lactate, Sodium Sesquicarbonate

Questions?

Call +1-574-855-2197

PRINCIPAL DISPLAY PANEL - 34 g Can Label

FOAMING
HAND
SANITIZER

antiseptic | rinse-free

Hubot healthcare